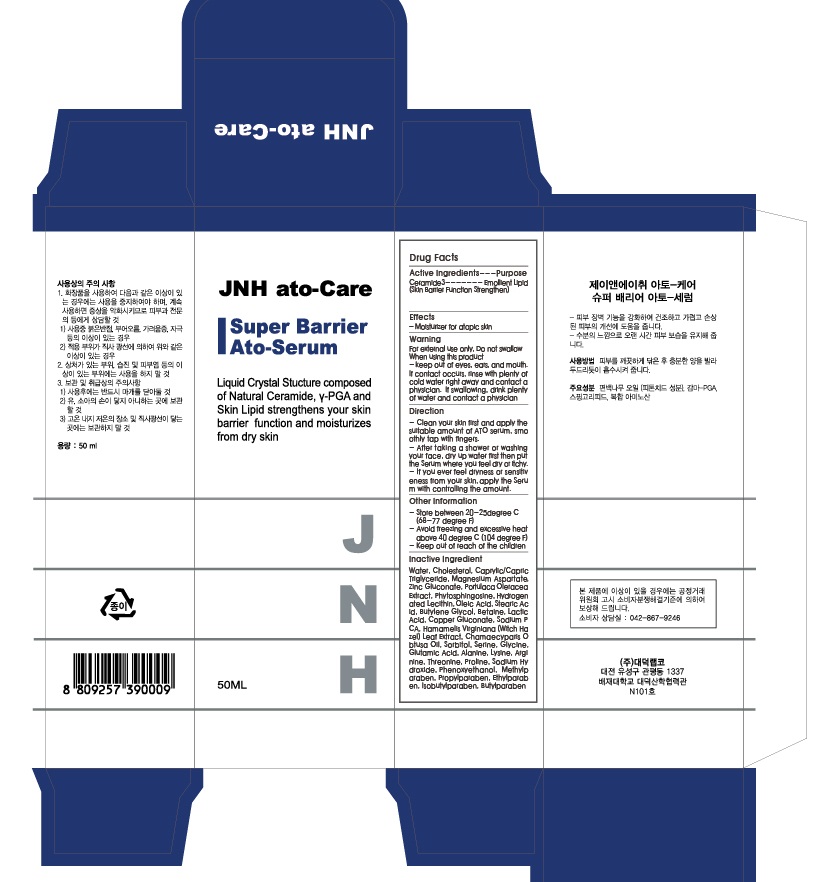 DRUG LABEL: JNH Ato-Care Super Barried ATO-Serum
                
NDC: 53010-3001 | Form: LIQUID
Manufacturer: Daeduck Lab Co., Ltd
Category: otc | Type: HUMAN OTC DRUG LABEL
Date: 20120824

ACTIVE INGREDIENTS: CERAMIDE 3 1.5 mg/50 mL
INACTIVE INGREDIENTS: CHOLESTEROL; MEDIUM-CHAIN TRIGLYCERIDES; MAGNESIUM ASPARTATE; ZINC GLUCONATE; PORTULACA OLERACEA WHOLE; PHYTOSPHINGOSINE; HYDROGENATED SOYBEAN LECITHIN; OLEIC ACID; STEARIC ACID; BUTYLENE GLYCOL; BETAINE; LACTIC ACID; COPPER GLUCONATE; SODIUM PYRROLIDONE CARBOXYLATE; WITCH HAZEL; CHAMAECYPARIS OBTUSA WOOD OIL; SORBITOL; SERINE; GLYCINE; ALANINE; LYSINE; ARGININE; THREONINE; PROLINE; SODIUM HYDROXIDE; PHENOXYETHANOL; METHYLPARABEN; PROPYLPARABEN; ETHYLPARABEN; ISOBUTYLPARABEN; BUTYLPARABEN

Drug Facts

ACTIVE INGREDIENT

ceramide 3

INACTIVE INGREDIENT

- Water - Cholesterol - Caprylic/Capric Triglyceride - Magnesium Aspartate - Zinc Gluconate - Portulaca Oleracea Extract – Phytosphingosine - Hydrogenated Lecithin - Oleic Acid - Stearic Acid - Butylene Glycol – Betaine - Lactic Acid - Copper Gluconate - Sodium PCA - Hamamelis Virginiana (Witch Hazel) Leaf Extract - Chamaecyparis Obtusa Oil - Sorbitol - Serine – Glycine - Glutamic Acid - Alanine - Lysine - Arginine - Threonine - Proline - Sodium Hydroxide - Phenoxyethanol - Methylparaben - Propylparaben - Ethylparaben - Isobutylparaben - Butylparaben

PURPOSE

moisturizer for atopic skin

keep out of reach of the children

INDICATIONS AND USAGE

- Clean your skin first and apply the suitable amount of ATO serum, smoothly tap with fingers.
- After taking a shower or washing your face, dry up water first then put the Serum where you feel dry or itchy.
- If you ever feel dryness or sensitiveness from your skin, apply the Serum with controlling the amount.

When using this product
- keep out of eyes, ears, and mouth. If contact occurs, rinse with plenty of cold water right away and contact a physician. If swallowing, drink plenty of water and contact a physician

DOSAGE AND ADMINISTRATION

for external use only